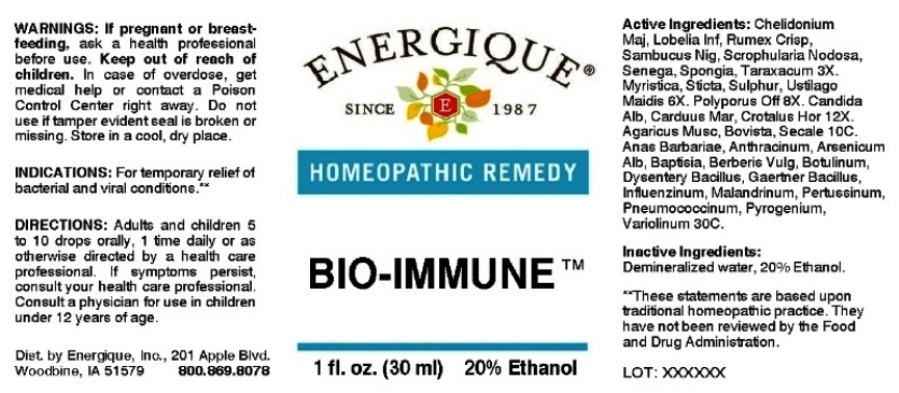 DRUG LABEL: Bio Immune
NDC: 44911-0269 | Form: LIQUID
Manufacturer: Energique, Inc.
Category: homeopathic | Type: HUMAN OTC DRUG LABEL
Date: 20161222

ACTIVE INGREDIENTS: CHELIDONIUM MAJUS 3 [hp_X]/1 mL; LOBELIA INFLATA 3 [hp_X]/1 mL; RUMEX CRISPUS ROOT 3 [hp_X]/1 mL; SAMBUCUS NIGRA FLOWERING TOP 3 [hp_X]/1 mL; SCROPHULARIA NODOSA 3 [hp_X]/1 mL; POLYGALA SENEGA ROOT 3 [hp_X]/1 mL; SPONGIA OFFICINALIS SKELETON, ROASTED 3 [hp_X]/1 mL; TARAXACUM OFFICINALE 3 [hp_X]/1 mL; VIROLA SEBIFERA RESIN 6 [hp_X]/1 mL; LOBARIA PULMONARIA 6 [hp_X]/1 mL; SULFUR 6 [hp_X]/1 mL; USTILAGO MAYDIS 6 [hp_X]/1 mL; LARICIFOMES OFFICINALIS FRUITING BODY 8 [hp_X]/1 mL; CANDIDA ALBICANS 12 [hp_X]/1 mL; MILK THISTLE 12 [hp_X]/1 mL; CROTALUS HORRIDUS HORRIDUS VENOM 12 [hp_X]/1 mL; AMANITA MUSCARIA FRUITING BODY 10 [hp_C]/1 mL; LYCOPERDON UTRIFORME FRUITING BODY 10 [hp_C]/1 mL; CLAVICEPS PURPUREA SCLEROTIUM 10 [hp_C]/1 mL; CAIRINA MOSCHATA HEART/LIVER AUTOLYSATE 30 [hp_C]/1 mL; BACILLUS ANTHRACIS IMMUNOSERUM RABBIT 30 [hp_C]/1 mL; ARSENIC TRIOXIDE 30 [hp_C]/1 mL; BAPTISIA TINCTORIA ROOT 30 [hp_C]/1 mL; BERBERIS VULGARIS ROOT BARK 30 [hp_C]/1 mL; BOTULINUM TOXIN TYPE A 30 [hp_C]/1 mL; SHIGELLA DYSENTERIAE 30 [hp_C]/1 mL; SALMONELLA ENTERICA SUBSP. ENTERICA SEROVAR ENTERITIDIS 30 [hp_C]/1 mL; INFLUENZA A VIRUS 30 [hp_C]/1 mL; INFLUENZA B VIRUS 30 [hp_C]/1 mL; VACCINIA VIRUS 30 [hp_C]/1 mL; HUMAN SPUTUM, BORDETELLA PERTUSSIS INFECTED 30 [hp_C]/1 mL; STREPTOCOCCUS PNEUMONIAE 30 [hp_C]/1 mL; RANCID BEEF 30 [hp_C]/1 mL; VACCINIA VIRUS STRAIN NEW YORK CITY BOARD OF HEALTH LIVE ANTIGEN 30 [hp_C]/1 mL
INACTIVE INGREDIENTS: WATER; ALCOHOL

DRUG FACTS:

ACTIVE INGREDIENTS:

Chelidonium Majus, Lobelia Inflata, Rumex Crispus, Sambucus Nigra, Scrophularia Nodosa, Senega Officinalis, Spongia Tosta, Taraxacum Officinale 3X. Myristica Sebifera, Sticta Pulmonaria, Sulphur, Ustilago Maidis 6X. Polyporus Officinalis, Candida Albicans, Carduus Marianus, Crotalus Horridus 12X. Agaricus Muscarius, Bovista, Secale Cornutum 10C. Anas Barbariae, Hepatis Et Cordis Extractum, Anthracinum, Arsenicum Album, Baptisia Tinctoria, Berberis Vulgaris, Botulinum, Dysentery Bacillus, Gaertner Bacillus, Influenzinum, Malandrinum, Pertussinum, Pneumococcinum, Pyrogenium, Variolinum 30C.

INDICATIONS:

For temporary relief of bacterial and viral conditions.**

**These statements are based upon traditional homeopathic practice. They have not been reviewed by the Food and Drug Administration.

WARNINGS:

If pregnant or breast-feeding, ask a health professional before use.

Keep out of reach of children. In case of overdose, get medical help or contact a Poison Control Center right away.

Do not use if tamper evident seal is broken or missing. Store in a cool, dry place.

Keep out of reach of children. In case of overdose, get medical help or contact a Poison Control Center right away.

DIRECTIONS:

Adults and children 5 to 10 drops orally, 1 time daily or as otherwise directed by a health care professional. If symptoms persist, consult your health care professional.

Consult a physician for use in children under 12 years of age.

INDICATIONS:

For temporary relief of bacterial and viral conditions.**

**These statements are based upon traditional homeopathic practice. They have not been reviewed by the Food and Drug Administration.

INACTIVE INGREDIENTS:

Demineralized water, 20% Ethanol.

QUESTIONS:

Dist. by Energique, Inc.
201 Apple Blvd
Woodbine, IA 51579 800-869-8078

PACKAGE LABEL DISPLAY:

ENERGIQUE

SINCE 1987

HOMEOPATHIC REMEDY

BIO-IMMUNE

1 FL. OZ. (30 ml)